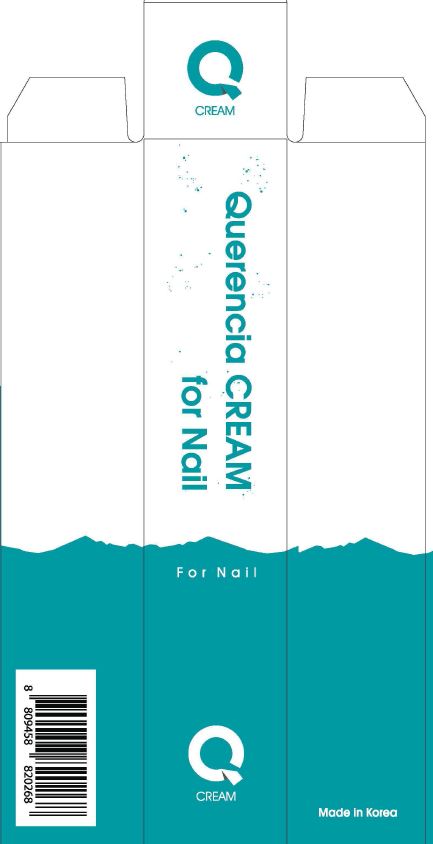 DRUG LABEL: Querencia CREAMfor Nail
NDC: 70488-0007 | Form: LIQUID
Manufacturer: MUSEE Cosmetic Co.,Ltd.
Category: otc | Type: HUMAN OTC DRUG LABEL
Date: 20190103

ACTIVE INGREDIENTS: GLYCERIN 8 g/100 mL
INACTIVE INGREDIENTS: WATER; SHEA BUTTER

Drug Facts

ACTIVE INGREDIENT

glycerin

INACTIVE INGREDIENT

water, ButyrospermumParkii (Shea Butter), Bentonite, SparassisCrispa Extract, Cetearyl Alcohol, Theobroma Cacao (Cocoa) Seed Butter, Cocos Nucifera (Coconut) Oil, Prunus Amygdalus Dulcis (Sweet Almond) Oil, Beeswax, Stearyl alcohol, 1,2-Hexanediol, Eucalyptus Globulus Leaf Oil, Rosmarinus Officinalis (Rosemary) Leaf Oil, Citrus AurantiumDulcis (Orange) Peel Oil, Glyceryl Stearate, Cetearyl Glucoside, Disodium EDTA

PURPOSE

Problematic nails and skin improvement moisturizer

keep out of reach of the children

INDICATIONS AND USAGE

Apply a proper amount to the entire nail and absorb it as a massage
It is recommended to use twice a day

WARNINGS

1. Do not use in the following cases(Eczema and scalp wounds)
2.Side Effects
1)Due to the use of this druf if rash, irritation, itching and symptopms of hypersnesitivity occur dicontinue use and consult your phamacisr or doctor
3.General Precautions
1)If in contact with the eyes, wash out thoroughty with water If the symptoms are servere, seek medical advice immediately
2)This product is for exeternal use only. Do not use for internal use
4.Storage and handling precautions
1)If possible, avoid direct sunlight and store in cool and area of low humidity
2)In order to maintain the quality of the product and avoid misuse
3)Avoid placing the product near fire and store out in reach of children

DOSAGE AND ADMINISTRATION

for topical use only